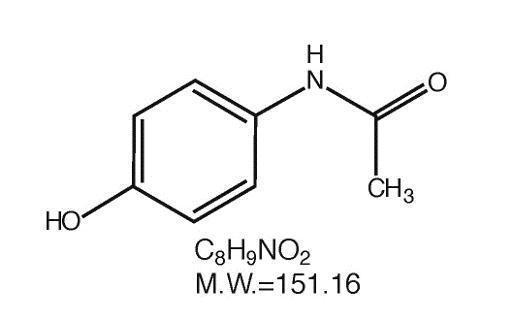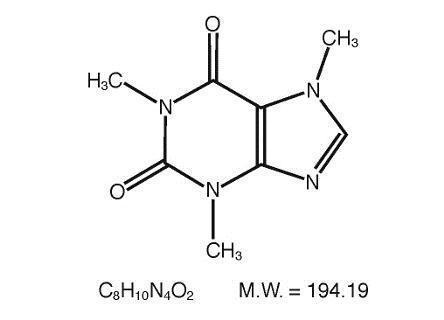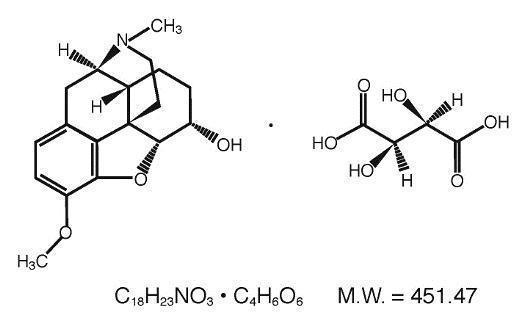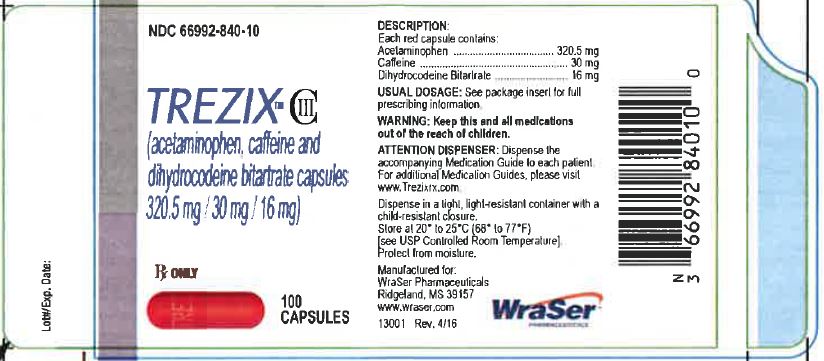 DRUG LABEL: Trezix
NDC: 66992-840 | Form: CAPSULE
Manufacturer: Wraser Llc
Category: prescription | Type: HUMAN PRESCRIPTION DRUG LABEL
Date: 20210203
DEA Schedule: CIII

ACTIVE INGREDIENTS: ACETAMINOPHEN 320.5 mg/1 1; CAFFEINE 30 mg/1 1; DIHYDROCODEINE BITARTRATE 16 mg/1 1
INACTIVE INGREDIENTS: CROSPOVIDONE; MAGNESIUM STEARATE; POVIDONE, UNSPECIFIED; STARCH, CORN; STEARIC ACID; FD&C RED NO. 40; GELATIN

TREZIX™ Capsules

Acetaminophen, Caffeine and Dihydrocodeine Bitartrate

320.5 mg / 30 mg / 16 mg
Rx Only CIII

BOXED WARNING

WARNING: ADDICTION, ABUSE, AND MISUSE; LIFE-THREATENING RESPIRATORY DEPRESSION; ACCIDENTAL INGESTION; ULTRA-RAPID METABOLISM OF CODEINE AND OTHER RISK FACTORS FOR LIFE-THREATENING RESPIRATORY DEPRESSION IN CHILDREN; NEONATAL OPIOID WITHDRAWAL SYNDROME; INTERACTIONS WITH DRUGS AFFECTING CYTOCHROME P450 ISOENYME; HEPTATOTOXICITY; and RISKS FROM CONCOMITANT USE WITH BENZODIAZEPINES OR OTHER CNS DEPRESSANTS

Addiction, Abuse and Misuse
TREZIX™ expose patients and other users to the risks of opioid addiction, abuse and misuse, which can lead to overdose and death. Assess each patient’s risk prior to prescribing TREZIX™, and monitor all patients regularly for the development of these behaviors and conditions [see WARNINGS].

Life-Threatening Respiratory Depression
Serious, life-threatening, or fatal respiratory depression may occur with use of TREZIX™. Monitor for respiratory depression, especially during initiation of TREZIX™ or following a dose increase [see WARNINGS].

Accidental Ingestion
Accidental ingestion of TREZIX™, especially by children, can result in a fatal overdose of TREZIX™ [see WARNINGS].

Ultra-Rapid Metabolism of Codeine and Other Risk Factors for Life-threatening Respiratory Depression in Children
Life-threatening respiratory depression and death have occurred in children who received codeine. Most of the reported cases occurred following tonsillectomy and/or adenoidectomy, and many of the children had evidence of being an ultra-rapid metabolizer of codeine due to CYP2D6 polymorphism [see WARNINGS and PRECAUTIONS]. TREZIXTM is contraindicated in children younger than 12 years of age and in children younger than 18 years of age following tonsillectomy and/or adenoidectomy [see CONTRAINDICATIONS]. Avoid the use of TREZIX™ in adolescents 12 to 18 years of age who have other risk factors that may increase their sensitivity to the respiratory depressant effects of codeine.

Neonatal Opioid Withdrawal Syndrome
Prolonged use of TREZIX™ during pregnancy can result in neonatal opioid withdrawal syndrome, which may be life-threatening if not recognized and treated, and requires management according to protocols developed by neonatology experts. If opioid use is required for a prolonged period in a pregnant woman, advise the patient of the risk of neonatal opioid withdrawal syndrome and ensure that appropriate treatment will be available [see WARNINGS].

Interactions with Drugs Affecting Cytochrome P450 Isoenzymes
The effects of concomitant use or discontinuation of cytochrome P450 3A4 inducers, 3A4 inhibitors, or 2D6 inhibitors with codeine are complex. Use of cytochrome P450 3A4 inducers, 3A4 inhibitors, or 2D6 inhibitors with TREZIX™ requires careful consideration of the effects on the parent drug, codeine, and the active metabolite, morphine[see WARNINGS and PRECAUTIONS]

Hepatotoxicity
Acetaminophen has been associated with cases of acute liver failure, at times resulting in liver transplant and death. Most of the cases of liver injury are associated with the use of acetaminophen at doses that exceed 4,000 milligrams per day, and often involve more than one acetaminophen-containing product [see WARNINGS].

Risks From Concomitant Use With Benzodiazepines Or Other CNS Depressants
Concomitant use of opioids with benzodiazepines or other central nervous system (CNS) depressants, including alcohol, may result in profound sedation, respiratory depression, coma, and death [see WARNINGS, PRECAUTIONS; Drug Interactions].

- Reserve concomitant prescribing of TREZIX™ and benzodiazepines or other CNS depressants for use in patients for whom alternative treatment options are inadequate.
- Limit dosages and durations to the minimum required.
- Follow patients for signs and symptoms of respiratory depression and sedation.

DESCRIPTION

TREZIX™ capsules are supplied in capsule form for oral administration.
Each red capsule contains:
Acetaminophen...........................................320.5 mg
Caffeine ..........................................................30 mg
Dihydrocodeine bitartrate ...............................16 mg

Acetaminophen (4'-hydroxyacetanilide), a slightly bitter, white, odorless, crystalline powder, is a non-opiate, non-salicylate analgesic and antipyretic. It has the following structural formula:

Caffeine (1,3,7-trimethylxanthine), a bitter, white crystalline powder or white glistening needles, is a central nervous system stimulant. It has the following structural formula:

Dihydrocodeine Bitartrate (4,5 _-epoxy-3-methoxy-17-methylmorphinan-6 _-ol (+)-tartrate), an odorless, fine white powder is an opioid analgesic. It has the following structural formula:
In addition, each capsule contains the following inactive ingredients: crospovidone, magnesium stearate, povidone, pregelatinized starch, stearic acid. The capsule is composed of FD&C Red #40, and gelatin. Imprinting ink is composed of ammonium hydroxide, isopropyl alcohol, n-butyl alcohol, pharmaceutical glaze (modified) in SD-45, propylene glycol, simethicone, and titanium dioxide.

CLINICAL PHARMACOLOGY

TREZIX™ capsules contain dihydrocodeine which is a semi-synthetic narcotic analgesic related to codeine, with multiple actions qualitatively similar to those of codeine; the most prominent of these involve the central nervous system and organs with smooth muscle components. The principal action of therapeutic value is analgesia.

This combination product also contains acetaminophen, a non-opiate, non-salicylate analgesic and antipyretic. This combination product contains caffeine as an analgesic adjuvant. Caffeine is also a CNS and cardiovascular stimulant.

Effects on the Endocrine System
Chronic use of opioids may influence the hypothalamic-pituitary-gonadal axis, leading to hormonal changes that may manifest as low libido, impotence, erectile dysfunction, amenorrhea, or infertility. The causal role of opioids in the clinical syndrome of hypogonadism is unknown because the various medical, physical, lifestyle, and psychological stressors that may influence gonadal hormone levels have not been adequately controlled for in studies conducted to date [see ADVERSE REACTIONS].

INDICATIONS AND USAGE

TREZIX™ (acetaminophen, caffeine, and dihydrocodeine bitartrate) capsules are indicated for the management of pain severe enough to require an opioid analgesic and for which alternative treatments are inadequate.

Limitations of Use
Because of the risks of addiction, abuse, and misuse, with opioids, even at recommended doses [see WARNINGS], reserve TREZIX™ for use in patients for whom alternative treatment options [e.g., non-opioid analgesics]

- Have not been tolerated, or are not expected to be tolerated,
- Have not provided adequate analgesia, or are not expected to provide adequate analgesia

CONTRAINDICATIONS

TREZIX™ is contraindicated for:

- All children younger than 12 years of age [see WARNINGS and PRECAUTIONS]
- Post-operative management in children younger than 18 years of age following tonsillectomy and/or adenoidectomy [see WARNINGS and PRECAUTIONS].
- TREZIXTM is also contraindicated in patients with:
- Significant respiratory depression [see WARNINGS]
- Acute or severe bronchial asthma in an unmonitored setting or in the absence of resuscitative equipment [see WARNINGS]
- Known or suspected gastrointestinal obstruction, including paralytic ileus [see WARNINGS]
- Hypersensitivity to codeine, acetaminophen, or any of the formulation excipients. (e.g., anaphylaxis) [see WARNINGS]

Dihydrocodeine-containing products are contraindicated for postoperative pain management in children who have undergone tonsillectomy and/or adenoidectomy.

This combination product is contraindicated in patients with hypersensitivity to dihydrocodeine, codeine, acetaminophen, caffeine, or any of the inactive components listed above, or any situation where opioids are contraindicated including significant respiratory depression (in unmonitored settings or in the absence of resuscitative equipment), acute or severe bronchial asthma or hypercapnia, and paralytic ileus.

WARNINGS

Addiction, Abuse, and Misuse
TREZIX™ contains dihydrocodeine bitartrate , a Schedule III controlled substance. As an opioid,
TREZIX™ exposes users to the risks of addiction, abuse, and misuse [see DRUG
ABUSE AND DEPENDENCE].

Although the risk of addiction in any individual is unknown, it can occur in patients appropriately prescribed TREZIX™. Addiction can occur at recommended dosages and if the drug is misused or abused

Assess each patient’s risk for opioid addiction, abuse, or misuse prior to prescribing TREZIX™, and monitor all patients receiving TREZIX™ for the development of these behaviors or conditions. Risks are increased in patients with a personal or family history of substance abuse (including drug or alcohol abuse or addiction) or mental illness (e.g., major depression). The potential for these risks should not, however, prevent the proper management of pain in any given patient. Patients at increased risk may be prescribed opioids such as TREZIX™, but use in such patients necessitates intensive counseling about the risks and proper use of TREZIX™ along with intensive monitoring for signs of addiction, abuse, and misuse.

Opioids are sought by drug abusers and people with addiction disorders and are subject to criminal diversion. Consider these risks when prescribing or dispensing TREZIX™ .Strategies to reduce these risks include prescribing the drug in the smallest appropriate quantity and advising the patient on the proper disposal of unused drug [see PRECAUTIONS; Information for Patients]. Contact local state professional licensing board or state controlled substances authority for information on how to prevent and detect abuse or diversion of this product.

Life-Threatening Respiratory Depression
Serious, life-threatening, or fatal respiratory depression has been reported with the use of
opioids, even when used as recommended. Respiratory depression, if not immediately
recognized and treated, may lead to respiratory arrest and death. Management of respiratory depression may include close observation, supportive measures, and use of opioid antagonists, depending on the patient’s clinical status [see OVERDOSAGE]. Carbon dioxide (CO2) retention from opioid-induced respiratory depression can exacerbate the sedating effects of opioids.

While serious, life-threatening, or fatal respiratory depression can occur at any time during the use of TREZIX™, the risk is greatest during the initiation of therapy or following a dosage increase. Monitor patients closely for respiratory depression, especially within the first 24-72 hours of initiating therapy with and following dosage increases of TREZIX™.

To reduce the risk of respiratory depression, proper dosing and titration of TREZIX™ are
essential [see DOSAGE AND ADMINISTRATION]. Overestimating the TREZIX™ dosage when converting patients from another opioid product can result in a fatal overdose with the first dose.

Accidental ingestion of TREZIX™, especially by children, can result in respiratory depression and death due to an overdose of dihydrocodeine bitartrate.

Ultra-Rapid Metabolism of Codeine and Other Risk Factors for Life-threatening Respiratory Depression in Children
Life-threatening respiratory depression and death have occurred in children who received codeine. Codeine is subject to variability in metabolism based upon CYP2D6 genotype (described below), which can lead to an increased exposure to the active metabolite morphine. Based upon post-marketing reports, children less than 12 years old appear to be more susceptible to the respiratory depressant effects of codeine, particularly if there are risk factors for respiratory depression. For example, many reported cases of death occurred in the post-operative period following tonsillectomy and/or adenoidectomy, and many of the children had evidence of being ultra-rapid metabolizers of codeine. Furthermore, children with obstructive sleep apnea who are treated with codeine for post-tonsillectomy and/or adenoidectomy pain may be particularly sensitive to its respiratory depressant effect. Because of the risk of life-threatening respiratory depression and death:

• TREZIX™ is contraindicated for all children younger than 12 years of age [see CONTRAINDICATIONS].

• TREZIX™ is contraindicated for post-operative management in pediatric patients younger than 18 years of age following tonsillectomy and/or adenoidectomy [see CONTRAINDICATIONS].

• Avoid the use of TREZIX™ in adolescents 12 to 18 years of age who have other risk factors that may increase their sensitivity to the respiratory depressant effects of codeine unless the benefits outweigh the risks. Risk factors include conditions associated with hypoventilation, such as postoperative status, obstructive sleep apnea, obesity, severe pulmonary disease, neuromuscular disease, and concomitant use of other medications that cause respiratory depression.

• As with adults, when prescribing codeine for adolescents, healthcare providers should choose the lowest effective dose for the shortest period of time and inform patients and caregivers about these risks and the signs of morphine overdose [see OVERDOSAGE].

Nursing Mothers
At least one death was reported in a nursing infant who was exposed to high levels of morphine in breast milk because the mother was an ultra-rapid metabolizer of codeine. Breastfeeding is not recommended during treatment with TREZIX™ [see PRECAUTIONS; Nursing Mothers].
CYP2D6 Genetic Variability: Ultra-rapid metabolizer
Some individuals may be ultra-rapid metabolizers because of a specific CYP2D6 genotype (e.g., gene duplications denoted as *1/*1xN or *1/*2xN). The prevalence of this CYP2D6 phenotype varies widely and has been estimated at 1 to 10% for Whites (European, North American), 3 to 4% for Blacks (African Americans), 1 to 2% for East Asians (Chinese, Japanese, Korean), and may be greater than 10% in certain ethnic groups (i.e., Oceanian, Northern African, Middle Eastern, Ashkenazi Jews, Puerto Rican). These individuals convert codeine into its active metabolite, morphine, more rapidly and completely than other people. This rapid conversion results in higher than expected serum morphine levels. Even at labeled dosage regimens, individuals who are ultra-rapid metabolizers may have life-threatening or fatal respiratory depression or experience signs of overdose (such as extreme sleepiness, confusion, or shallow breathing) [see OVERDOSAGE]. Therefore, individuals who are ultra-rapid metabolizers should not use codeine.

Neonatal Opioid Withdrawal Syndrome
Prolonged use of TREZIX™ during pregnancy can result in withdrawal in the neonate. Neonatal opioid withdrawal syndrome, unlike opioid withdrawal syndrome in adults, may be life-threatening if not recognized and treated, and requires management according to protocols developed by neonatology experts. If opioid use is required for a prolonged period in a pregnant woman, advise the patient of the risk of neonatal opioid withdrawal syndrome and ensure that appropriate treatment will be available [see PRECAUTIONS; Information for Patients, Pregnancy].

Interactions with Drugs Affecting Cytochrome P450 Isoenzymes
The effects of concomitant use or discontinuation of cytochrome P450 3A4 inducers, 3A4 inhibitors, or 2D6 inhibitors with codeine are complex. Use of cytochrome P450 3A4 inducers, 3A4 inhibitors, or 2D6 inhibitors with TREZIX™ requires careful consideration of the effects on the parent drug, codeine, and the active metabolite, morphine.

- Cytochrome P450 3A4 Interaction

The concomitant use of TREZIX™ with all cytochrome P450 3A4 inhibitors , such as macrolide antibiotics (e.g., erythromycin), azole-antifungal agents (e.g., ketoconazole), and protease inhibitors (e.g., ritonavir) or discontinuation of a cytochrome P450 3A4 inducer such as rifampin, carbamazepine, and phenytoin, may result in an increase in codeine plasma concentrations with subsequently greater metabolism by cytochrome P450 2D6, resulting in greater morphine levels, which could increase or prolong adverse reactions and may cause potentially fatal respiratory depression.

The concomitant use of TREZIX™ with all cytochrome P450 3A4 inducers or discontinuation of a cytochrome P450 3A4 inhibitor may result in lower codeine levels, greater norcodeine levels, and less metabolism via 2D6 with resultant lower morphine levels. This may be associated with a decrease in efficacy, and in some patients, may result in signs and symptoms of opioid withdrawal.

Follow patients receiving TREZIX™ and any CYP3A4 inhibitor or inducer for signs and symptoms that may reflect opioid toxicity and opioid withdrawal when TREZIX™ are used in conjunction with inhibitors and inducers of CYP3A4.

If concomitant use of a CYP3A4 inhibitor is necessary or if a CYP3A4 inducer is discontinued, consider dosage reduction of TREZIX™ until stable drug effects are achieved. Monitor patients for respiratory depression and sedation at frequent intervals.

If concomitant use of a CYP3A4 inducer is necessary or if a CYP3A4 inhibitor is discontinued, consider increasing the TREZIX™ dosage until stable drug effects are achieved. Monitor for signs of opioid withdrawal [see PRECAUTIONS, Drug Interactions].

- Risks of Concomitant Use or Discontinuation of Cytochrome P450 2D6 Inhibitors

The concomitant use of TREZIX™ with all cytochrome P450 2D6 inhibitors (e.g., amiodarone, quinidine) may result in an increase in codeine plasma concentrations and a decrease in active metabolite morphine plasma concentration which could result in an analgesic efficacy reduction or symptoms of opioid withdrawal.

Discontinuation of a concomitantly used cytochrome P450 2D6 inhibitor may result in a decrease in codeine plasma concentration and an increase in active metabolite morphine plasma concentration which could which could increase or prolong adverse reactions and may cause potentially fatal respiratory depression.

Follow patients receiving TREZIX™ and any CYP2D6 inhibitor for signs and symptoms that may reflect opioid toxicity and opioid withdrawal when TREZIX™ are used in conjunction with inhibitors of CYP2D6. If concomitant use with a CYP2D6 inhibitor is necessary, follow the patient for signs of reduced efficacy or opioid withdrawal and consider increasing the TREZIX™ dosage. After stopping use of a CYP2D6 inhibitor, consider reducing the TREZIX™ dosage and follow the patient for signs and symptoms of respiratory depression or sedation [see PRECAUTIONS; Drug Interactions].

Hepatotoxicity
Acetaminophen has been associated with cases of acute liver failure, at times resulting in liver transplant and death. Most of the cases of liver injury are associated with the use of acetaminophen at doses that exceed 4000 milligrams per day, and often involve more than one acetaminophen containing product. The excessive intake of acetaminophen may be intentional to cause self-harm or unintentional as patients attempt to obtain more pain relief or unknowingly take other acetaminophen-containing products. The risk of acute liver failure is higher in individuals with underlying liver disease and in individuals who ingest alcohol while taking acetaminophen. Instruct patients to look for acetaminophen or APAP on package labels and not to use more than one product that contains acetaminophen. Instruct patients to seek medical attention immediately upon ingestion of more than 4000 milligrams of acetaminophen per day, even if they feel well.

Risks from Concomitant Use with Benzodiazepines or Other CNS Depressants
Profound sedation, respiratory depression, coma, and death may result from the concomitant use of TREZIX™ with benzodiazepines or other CNS depressants (e.g., non-benzodiazepine sedatives/hypnotics, anxiolytics, tranquilizers, muscle relaxants, general anesthetics, antipsychotics, other opioids, alcohol). Because of these risks, reserve concomitant prescribing of these drugs for use in patients for whom alternative treatment options are inadequate.

Observational studies have demonstrated that concomitant use of opioid analgesics and benzodiazepines increases the risk of drug-related mortality compared to use of opioid analgesics alone. Because of similar pharmacological properties, it is reasonable to expect similar risk with the concomitant use of other CNS depressant drugs with opioid analgesics [see PRECAUTIONS; Drug Interactions].

If the decision is made to prescribe a benzodiazepine or other CNS depressant concomitantly with an opioid analgesic, prescribe the lowest effective dosages and minimum durations of concomitant use. In patients already receiving an opioid analgesic, prescribe a lower initial dose of the benzodiazepine or other CNS depressant than indicated in the absence of an opioid, and titrate based on clinical response. If an opioid analgesic is initiated in a patient already taking a benzodiazepine or other CNS depressant, prescribe a lower initial dose of the opioid analgesic, and titrate based on clinical response. Follow patients closely for signs and symptoms of respiratory depression and sedation.

Advise both patients and caregivers about the risks of respiratory depression and sedation when TREZIX™ is used with benzodiazepines or other CNS depressants (including alcohol and illicit drugs). Advise patients not to drive or operate heavy machinery until the effects of concomitant use of the benzodiazepine or other CNS depressant have been determined. Screen
patients for risk of substance use disorders, including opioid abuse and misuse, and warn them of the risk for overdose and death associated with the use of additional CNS depressants including alcohol and illicit drugs [see PRECAUTIONS; Drug Interactions and PRECAUTIONS; Information for Patients].

Life-Threatening Respiratory Depression in Patients with Chronic Pulmonary Disease or in Elderly, Cachectic, or Debilitated Patients
The use of TREZIX™ in patients with acute or severe bronchial asthma in an unmonitored setting or in the absence of resuscitative equipment is contraindicated.

Patients with Chronic Pulmonary Disease: - TREZIX™ treated patients with significant
chronic obstructive pulmonary disease or cor pulmonale, and those with a substantially
decreased respiratory reserve, hypoxia, hypercapnia, or pre-existing respiratory depression are at increased risk of decreased respiratory drive including apnea, even at recommended dosages of TREZIX™ [see WARNINGS].

Elderly, Cachetic, or Debilitated Patients: Life-threatening respiratory depression is more likely to occur in elderly, cachectic, or debilitated patients because they may have altered pharmacokinetics or altered clearance compared to younger, healthier patients [see
WARNINGS].

Monitor such patients closely, particularly when initiating and titrating TREZIX™ and
when TREZIX™ is given concomitantly with other drugs that depress respiration [see
WARNINGS]. Alternatively, consider the use of non-opioid analgesics in these patients.

Adrenal Insufficiency
Cases of adrenal insufficiency have been reported with opioid use, more often following greater than 1 month of use. Presentation of adrenal insufficiency may include non-specific symptoms and signs including nausea, vomiting, anorexia, fatigue, weakness, dizziness, and low blood pressure. If adrenal insufficiency is suspected, confirm the diagnosis with diagnostic testing as soon as possible. If adrenal insufficiency is diagnosed, treat with physiologic replacement doses of corticosteroids. Wean the patient off of the opioid to allow adrenal function to recover and continue corticosteroid treatment until adrenal function recovers. Other opioids may be tried as some cases reported use of a different opioid without recurrence of adrenal insufficiency. The information available does not identify any particular opioids as being more likely to be
associated with adrenal insufficiency

Serious Skin Reactions
Rarely, acetaminophen may cause serious skin reactions such as acute generalized exanthematous pustulosis (AGEP), Stevens-Johnson Syndrome (SJS), and toxic epidermal necrolysis (TEN), which can be fatal. Patients should be informed about the signs of serious skin reactions, and use of the drug should be discontinued at the first appearance of skin rash or any other sign of hypersensitivity.

Usage in Ambulatory Patients
Dihydrocodeine may impair the mental and/or physical abilities required for the performance of potentially hazardous tasks such as driving a car or operating machinery.

Respiratory Depression
Respiratory depression is the most dangerous acute reaction produced by opioid agonist preparations, although it is rarely severe with usual doses. Opioids decrease the respiratory rate, tidal volume, minute ventilation, and sensitivity to carbon dioxide. Respiratory depression occurs most frequently in elderly or debilitated patients, usually after large initial doses in nontolerant patients, or when opioids are given in conjunction with other agents that depress respiration. This combination product should be used with caution in patients with significant chronic obstructivepulmonary disease or cor pulmonale and in patients with a substantially decreased respiratory reserve, hypoxia hypercapnia, or respiratory depression. In such patients, alternative non-opioid analgesics should be considered, and opioids should be administered only under careful medical supervision at the lowest effective dose.

Head Injury
This combination product should be used cautiously in the presence of head injury or increased intracranial pressure. The effects of opioids on pupillary response and consciousness may obscure neurologic signs of increases in intracranial pressure in patients with head injuries. The respiratory depressant effects including carbon dioxide retention and secondary elevation of cerebrospinal fluid pressure may be markedly exaggerated in the presence of head injury, intracranial lesions, or other causes of increased intracranial pressures.

Hypersensitivity/Anaphylaxis
There have been post-marketing reports of hypersensitivity and anaphylaxis associated with use of acetaminophen. Clinical signs included swelling of the face, mouth, and throat, respiratory distress, urticaria, rash, pruritus, and vomiting. There were infrequent reports of life-threatening anaphylaxis requiring emergency medical attention. Instruct patients to discontinue TREZIX™ immediately and seek medical care if they experience these symptoms. Do not prescribe TREZIX™ for patients with acetaminophen allergy.

Hypotensive Effect
Dihydrocodeine, like all opioid analgesics, may cause hypotension in patients whose ability to maintain blood pressure has been compromised by a depleted blood volume or who receive concurrent therapy with drugs such as phenothiazines or other agents which compromise vasomotor tone. Acetaminophen, caffeine and dihydrocodeine bitartrate capsules may produce orthostatic hypotension in ambulatory patients. This combination product should be administered with caution to patients in circulatory shock, since vasodilation produced by the drug may further reduce cardiac output and blood pressure.

Drug Dependence
Dihydrocodeine can produce drug dependence of the codeine type and has the potential of being abused [see DRUG ABUSE AND DEPENDENCE].

PRECAUTIONS

General

Selection of patients for treatment with TREZIX™ (acetaminophen, caffeine, and dihydrocodeine bitartrate) capsules should be governed by the same principles that apply to the use of similar opioid/non-opioid fixed combination analgesics. As with any such opioid analgesic, the dosing regimen should be adjusted for each patient [see DOSAGE AND ADMINISTRATION]. This combination product should be used with caution in elderly or debilitated patients or those with any of the following conditions: acute alcoholism; adrenocortical insufficiency (e.g., Addison's disease); asthma; central nervous system depression or coma; chronic obstructive pulmonary disease; decreased respiratory reserve (including emphysema, severe obesity, cor pulmonale, or kyphoscoliosis); delirium tremens; head injury; hypotension; increased intracranial pressure; myxedema or hypothyroidism; prostatic hypertrophy or urethral stricture; and toxic psychosis. The benefits and risks of using opioids in patients taking monoamine oxidase inhibitors and in those with a history of drug abuse should be carefully considered. The administration of an analgesic containing an opioid may obscure the diagnosis or clinical course in patients with acute abdominal conditions. This combination product may aggravate convulsions in patients with convulsive disorders and, like all opioids, may induce or aggravate seizures in some clinical settings.

Acetaminophen is relatively non-toxic at therapeutic doses, but should be used with caution in patients with severe renal or hepatic disease. Care should be observed when using large doses of acetaminophen in malnourished patients or those with a history of chronic alcohol abuse because they may be more susceptible to hepatic damage similar to that observed with toxic overdosage. Caffeine in high doses may produce central nervous system and cardiovascular stimulation and gastrointestinal irritation.

Information for Patients/Caregivers

Addiction, Abuse, and Misuse
Inform patients that the use of TREZIX™ even when taken as recommended, can result
in addiction, abuse, and misuse, which can lead to overdose and death [see WARNINGS]. Instruct patients not to share TREZIX™ with others and to take steps to protect TREZIX™ from theft or misuse.

Life-Threatening Respiratory Depression
Inform patients of the risk of life-threatening respiratory depression, including information that the risk is greatest when starting TREZIX™ or when the dosage is increased, and that it can occur even at recommended dosages [see WARNINGS]. Advise patients how to recognize respiratory depression and to seek medical attention if breathing difficulties develop.

Accidental Ingestion
Inform patients that accidental ingestion, especially by children, may result in respiratory depression or death [see WARNINGS]. Instruct patients to take steps to store TREZIX™ securely and to dispose of unused TREZIX™.

Ultra-Rapid Metabolism of Codeine and Other Risk Factors for Life-threatening Respiratory Depression in Children
Advise patients that TREZIX™ is contraindicated in all in children younger than 12 years of age and in children younger than 18 years following tonsillectomy and/or adenoidectomy. Advise caregivers of children ages 12 to 18 years of age receiving TREZIX™ to monitor for signs of respiratory depression [see WARNINGS].

Interactions with Benzodiazepines and Other CNS Depressants
Inform patients and caregivers that potentially fatal additive effects may occur if
TREZIX™ is used with benzodiazepines or other CNS depressants, including alcohol, and not to use these concomitantly unless supervised by a health care provider [see WARNINGS and PRECAUTIONS; Drug Interactions].

Serotonin Syndrome
Inform patients that TREZIX™ could cause a rare but potentially life-threatening condition resulting from concomitant administration of serotonergic drugs. Warn patients of the symptoms of serotonin syndrome and to seek medical attention right away if symptoms develop.

Instruct patients to inform their physicians if they are taking, or plan to take serotonergic medications [see PRECAUTIONS; Drug Interactions].

Adrenal Insufficiency
Inform patients that TREZIX™ could cause adrenal insufficiency, a potentially life threatening condition. Adrenal insufficiency may present with non-specific symptoms and signs such as nausea, vomiting, anorexia, fatigue, weakness, dizziness, and low blood pressure. Advise patients to seek medical attention if they experience a constellation of these symptoms [see WARNINGS].

Important Administration Instructions
Instruct patients how to properly take TREZIX™ [see DOSAGE AND ADMINISTRATION].
• Advise patients not to adjust the dose of TREZIX™ without consulting a physician or other healthcare professional.
• If patients have been receiving treatment with TREZIX™ for more than a few weeks and cessation of therapy is indicated, counsel them on the importance of safely tapering the dose and that abruptly discontinuing the medication could precipitate withdrawal symptoms. Provide a dose schedule to accomplish a gradual discontinuation of the medication [see Warnings].

Pregnancy

Neonatal Opioid Withdrawal Syndrome
Inform female patients of reproductive potential that prolonged use of TREZIX™ during pregnancy can result in neonatal opioid withdrawal syndrome, which may be life-threatening if not recognized and treated [see WARNINGS, PRECAUTIONS; Pregnancy]

Embryo-Fetal Toxicity
Inform female patients of reproductive potential that TREZIX™ can cause fetal harm and to inform the prescriber of a known or suspected pregnancy [see PRECAUTIONS; Pregnancy].

Lactation
Advise woment that breastfeeding is not recommended during treatment with TREZIXTM [see PRECAUTIONS; Nursing Mothers].

Disposal of Unused TREZIX™
Advise patients to properly dispose of unused TREZIX™. Advise patients to throw the drug in the household trash following these steps.

1. Remove them from their original containers and mix them with an undesirable substance, such as used coffee grounds or kitty litter (this makes the drug less appealing to children and pets, and unrecognizable to people who may intentionally go through the trash seeking drugs).
2. Place the mixture in a sealable bag, empty can, or other container to prevent the drug from leaking or breaking out of a garbage bag, or to dispose of in accordance with the local state guidelines and/or regulations.

Patients receiving TREZIX™ capsules should be given the following information:

1. Do not take TREZIX™ if you are allergic to any of its ingredients. If you develop signs of allergy such as a rash or difficulty breathing stop taking TREZIX™ and contact your healthcare provider immediately.
2. Do not take more than 4000 milligrams of acetaminophen per day. Call your doctor if you took more than the recommended dose.
3. Patients should be advised that TREZIX™ capsules may impair the mental or physical abilities required for the performance of potentially hazardous tasks such as driving a car or operating machinery.
4. Patients should be advised to report adverse experiences occurring during therapy.
5. Patients should be advised not to adjust the dose of TREZIX™ capsules without consulting the prescribing professional.
6. Patients should be advised that TREZIX™ capsules are a potential drug of abuse. They should protect it from theft, and it should never be given to anyone other than the individual for whom it was prescribed.
7. Advise patients that some people have a genetic variation that results in dihydrocodeine changing into dihydromorphine more rapidly and completely than other people. Most people are unaware of whether they are an ultra-rapid dihydrocodeine metabolizer or not. These higher-than-normal levels of dihydromorphine in the blood may lead to life-threatening or fatal respiratory depression or signs of overdose such as extreme sleepiness, confusion, or shallow breathing. Children with this genetic variation who were prescribed codeine after tonsillectomy and/or adenoidectomy for obstructive sleep apnea may be at greatest risk based on reports of several deaths in this population due to respiratory depression. Dihydrocodeine-containing products are contraindicated in all children who undergo tonsillectomy and/or adenoidectomy.

Advise caregivers of children receiving dihydrocodeine-containing products for other reasons to monitor for signs of respiratory depression.

Drug Interactions

CYP2D6 InhibitorsDihydrocodeine in TREZIX™ is metabolized by CYP2D6 to form dihydromorphine . The concomitant use of TREZIX™ and CYP2D6 inhibitors (e.g., quinidine, fluoxetine, paroxetine, fluoxetine, bupropion, quinidine) can increase the plasma concentration of dihydrocodeine, but can decrease the plasma concentration of active metabolite dihydromorphine which could result in reduced analgesic efficacy or symptoms of opioid withdrawal, particularly when an inhibitor is added after a stable dose of TREZIX™ is achieved.

After stopping a CYP2D6 inhibitor, as the effects of the inhibitor decline, the dihydrocodeine plasma concentration will decrease but the active metabolite dihydromorphine plasma concentration will increase, which could increase or prolong adverse reactions and may cause potentially fatal respiratory depression. If concomitant use with a CYP2D6 inhibitor is necessary or if a CYP2D6 inhibitor is discontinued after concomitant use, consider dosage adjustment of TREZIX™ and monitor patients closely at frequent intervals. If concomitant use with CYP2D6 inhibitors is necessary, follow the patient for reduced efficacy or signs and symptoms of opioid withdrawal and consider increasing the TREZIX™ as needed. After stopping use of a CYP2D6 inhibitor, consider reducing the TREZIX™ and monitor the patient for signs and symptoms of
respiratory depression or sedation

CYP3A4 Inhibitors
The concomitant use of TREZIX™ with CYP3A4 inhibitors such as macrolide antibiotics (e.g., erythromycin), azole-antifungal agents (e.g. ketoconazole), and protease inhibitors (e.g., ritonavir), may result in an increase in dihydrocodeine plasma concentration with subsequently greater metabolism by cytochrome CYP2D6, resulting in greater dihydromorphine levels, which could increase or prolong adverse reactions and may cause potentially fatal respiratory depression, particularly when an inhibitor is added after a stable dose of TREZIX™ is achieved.

After stopping a CYP3A4 inhibitor, as the effects of the inhibitor decline, it may result in lower dihydrocodeine plasma levels, greater dihydronorcodeine levels, and less metabolism via 2D6 with resultant lower dihyromorphine levels, resulting in decreased opioid efficacy or a withdrawal syndrome in patients who had developed physical dependence to dihydrocodeine. If concomitant use with CYP3A4 inhibitor is necessary, consider dosage reduction of TREZIX™ until stable drug effects are achieved. Monitor patients for respiratory depression and sedation at frequent intervals.

If a CYP3A4 inhibitor is discontinued, consider increasing the TREZIX™ dosage until stable drug effects are achieved. Monitor for signs of opioid withdrawal.

CYP3A4 Inducers
The concomitant use of TREZIX™ and CYP3A4 inducers (e.g., rifampin, carbamazepine, phenytoin), can result in lower dihydrocodeine levels, greater dihydronorcodeine levels, and less metabolism via 2D6 with resultant lower dihyromorphine levels, resulting in decreased efficacy or a withdrawal syndrome in patients who had developed physical dependence to dihydrocodeine.

After stopping a CYP3A4 inducer, as the effects of the inhibitor decline, the dihydrocodeine plasma concentration may increase with subsequently greater metabolism by cytochrome CYP2D6, resulting in greater dihyromorphine levels, which could increase or prolong both the therapeutic effects and adverse reactions, and may cause serious respiratory depression.

If concomitant use with CYP3A4 inducer is necessary, follow the patient for reduced efficacy and signs of opioid withdrawal and consider increasing the TREZIX™ dosage as needed.

If a CYP3A4 inducer is discontinued, consider TREZIX™ dosage reduction and monitor for signs of respiratory depression and sedation at frequent intervals.

Benzodiazepines and Other Central Nervous System (CNS) Depressants
Due to additive pharmacologic effect, the concomitant use of benzodiazepines or other CNS depressants, including alcohol, and other sedatives/hypnotics, anxiolytics, tranquilizers, muscle relaxants, general anesthetics, antipsychotics and other opioids, can increase the risk of hypotension, respiratory depression, profound sedation, coma, and death. .

Reserve concomitant prescribing of these drugs for use in patients for whom alternative treatment options are inadequate. Limit dosages and durations to the minimum required. Follow patients closely for signs of respiratory depression and sedation [see WARNINGS].

Serotonergic Drugs
The concomitant use of opioids with other drugs that affect the serotonergic neurotransmitter system, such as selective serotonin reuptake inhibitors (SSRIs), serotonin and norepinephrine reuptake inhibitors (SNRIs), tricyclic antidepressants (TCAs), triptans, 5-HT3 receptor antagonists, drugs that effect the serotonin neurotransmitter system (e.g., mirtazapine, trazodone, tramadol), and monoamine oxidase (MAO) inhibitors (used to treat psychiatric disorders and also others, such as linezolid and intravenous methylene blue) [see PRECAUTIONS; Information for Patients].

If concomitant use is warranted, carefully observe the patient, particularly during treatment initiation and dose adjustment. Discontinue TREZIX™ immediately if serotonin syndrome is suspected.

Dihydrocodeine with Monoamine Oxidase Inhibitors
Dihydrocodeine, like all opioid analgesics, interacts with monoamine oxidase inhibitors causing central nervous system excitation and hypertension.

Dihydrocodeine with Mixed Agonist/Antagonist Opioid Analgesics
Agonist/antagonist analgesics (i.e., pentazocine, nalbuphine, butorphanol and buprenorphine) may reduce the analgesic effect of this combination product.

Acetaminophen Drug Interactions
Chronic and excessive consumption of alcohol may increase the hepatotoxic risk of acetaminophen. The potential for hepatotoxicity with acetaminophen also may be increased in patients receiving anticonvulsants that induce hepatic microsomal enzymes (including phenytoin, barbiturates, and carbamazepine) or isoniazide. Chronic ingestion of large doses of acetaminophen may slightly potentiate the effects of warfarin-and indandione-derivative anticoagulants. Severe hypothermia is possible in patients receiving acetaminophen concomitantly with phenothiazines.

Caffeine Drug Interactions
Caffeine may enhance the cardiac inotropic effects of beta-adrenergic stimulating agents. Co-administration of caffeine and disulfiram may lead to a substantial decrease in caffeine clearance. Caffeine may increase the metabolism of other drugs such as phenobarbital and aspirin. Caffeine accumulation may occur when products or foods containing caffeine are consumed concomitantly with quinolones such as ciprofloxacin.

Carcinogenesis, Mutagenesis, Impairment of Fertility

Infertility
Chronic use of opioids may cause reduced fertility in females and males of reproductive potential. It is not known whether these effects on fertility are reversible [see ADVERSE REACTIONS].

Pregnancy

Teratogenic Effects – Pregnancy Category C.
Animal reproduction studies have not been conducted with TREZIX™ (acetaminophen, caffeine, and dihydrocodeine bitartrate) capsules. It is also not known whether this combination product can cause fetal harm when administered to pregnant women or can affect reproduction capacity in males and females. This combination product should be given to pregnant women only if clearly needed, especially during the first trimester.

Fetal/Neonatal Adverse Reactions
Prolonged use of opioid analgesics during pregnancy for medical or nonmedical purposes can result in physical dependence in the neonate and neonatal opioid withdrawal syndrome shortly after birth.

Neonatal opioid withdrawal syndrome presents as irritability, hyperactivity and abnormal sleep pattern, high pitched cry, tremor, vomiting, diarrhea and failure to gain weight. The onset, duration, and severity of neonatal opioid withdrawal syndrome vary based on the specific opioid used, duration of use, timing and amount of last maternal use, and rate of elimination of the drug by the newborn. Observe newborns for symptoms of neonatal opioid withdrawal syndrome and manage accordingly [see WARNINGS].

Labor and Delivery

Opioids cross the placenta and may produce respiratory depression and psycho-physiologic effects in neonates. An opioid antagonist, such as naloxone, must be available for reversal of opioid-induced respiratory depression in the neonate. TREZIX™ is not recommended for use in pregnant women during or immediately prior to labor, when other analgesic techniques are more appropriate. Opioid analgesics, including TREZIX™, and can prolong labor through actions which temporarily reduce the strength, duration, and frequency of uterine contractions. However, this effect is not consistent and may be offset by an increased rate of cervical dilation, which tends to shorten labor. Monitor neonates exposed to opioid analgesics during labor for signs of excess sedation and respiratory depression.

Nursing Mothers

Dihydrocodeine bitartrate and its active metabolite, morphine, are present in human milk. There are published studies and cases that have reported excessive sedation, respiratory depression, and death in infants exposed to codeine via breast milk. Women who are ultra-rapid metabolizers of dihydrocodeine achieve higher than expected serum levels of morphine, potentially leading to higher levels of morphine in breast milk that can be dangerous in their breastfed infants. In women with normal dihydrocodeine metabolism (normal CYP2D6 activity), the amount of dihydrocodeine secreted into human milk is low and dose-dependent. There is no information on the effects of the dihydrocodeine on milk production. Because of the potential for serious adverse reactions, including excess sedation, respiratory depression, and death in a breastfed infant, advise patients that breastfeeding is not recommended during treatment with TREZIX™ [see WARNINGS].

Clinical Considerations

If Infants are exposed to TREZIXTM through breast milk, they should be monitored for excess sedation and respiratory depression. Withdrawal symptoms can occur in breastfed infants when maternal administration of an opioid analgesic is stopped, or when breast-feeding is stopped.

Acetaminophen and caffeine are also excreted in breast milk in small amounts. Because of the potential for serious adverse reactions in nursing infants from this combination product, a decision should be made whether to discontinue nursing or to discontinue the drug, taking into account the importance of the drug to the mother.

Pediatric Use

Safety and effectiveness of TREZIX™ in pediatric patients have not been established.

Life-threatening respiratory depression and death have occurred in children who received codeine [see WARNINGS]. In most of the reported cases, these events followed tonsillectomy and/or adenoidectomy and many of the children had evidence of being ultra-rapid metabolizers of codeine (i.e., multiple copies of the gene for cytochrome P450 isoenzyme 2D6 or high morphine concentrations). Children with sleep apnea may be particularly sensitive to the respiratory depressant effects of codeine because of the risk of life-threatening respiratory depression and death:

- TREZIXTM is contraindicated for all children younger than 12 years of age [see CONTRAINDICATIONS].
- TREZIXTM is contraindicated for post-operative pain management in pediatric patients of any age undergoing tonsillectomy and/or adenoidectomy [see CONTRAINDICATIONS].
- Avoid the use of TREZIX™ in adolescents 12 to 18 years of age who have other risk factors that may increase their sensitivity to the respiratory depressant effects of codeine unless the benefits outweigh the risks. Risk factors include conditions associated with
  hypoventilation, such as postoperative status, obstructive sleep apnea, obesity, severe pulmonary disease, neuromuscular disease, and
  concomitant use of other medications that cause respiratory depression [see WARNINGS].

Geriatric Use

Elderly patients (aged 65 years or older) may have increased sensitivity to TREZIX™. In general, use caution when selecting a dosage for an elderly patient, usually starting at the low end of the dosing range, reflecting the greater frequency of decreased hepatic, renal, or cardiac function and of concomitant disease or other drug therapy.

Respiratory depression is the chief risk for elderly patients treated with opioids, and has occurred after large initial doses were administered to patients who were not opioid-tolerant or when opioids were co-administered with other agents that depress respiration. Titrate the dosage of TREZIX™ slowly in geriatric patients and monitor closely for signs of central nervous system and central nervous system depression [see WARNINGS].

Hepatic Impairment

TREZIX™ (acetaminophen, caffeine, and dihydrocodeine bitartrate) capsules should be given with caution to patients with hepatic insufficiency. Since dihydrocodeine is metabolized by the liver and since acetaminophen potentially causes hepatotoxicity, the effects of this combination product should be monitored closely in such patients.

Renal Impairment

TREZIX™ (acetaminophen, caffeine, and dihydrocodeine bitartrate) capsules should be used with caution and at reduced dosage in the presence of impaired renal function.

Pancreatic/Biliary Tract Disease

Opioids may cause spasms of the sphincter of Oddi and should be used with caution in patients with biliary tract disease including pancreatitis.

ADVERSE REACTIONS

Dihydrocodeine:
The most frequently observed adverse reactions include light-headedness, dizziness, drowsiness, headache, fatigue, sedation, sweating, nausea, vomiting, constipation, pruritus, and skin reactions. With the exception of constipation, tolerance develops to most of these effects. Other reactions that have been observed with dihydrocodeine or other opioids include respiratory depression, orthostatic hypotension, cough suppression, confusion, diarrhea, miosis, abdominal pain, dry mouth, indigestion, anorexia, spasm of biliary tract, and urinary retention. Physical and psychological dependence are possibilities. Hypersensitivity reactions (including anaphylactoid reactions), hallucinations, vivid dreams, granulomatous interstitial nephritis, severe narcosis and acute renal failure have been reported rarely during dihydrocodeine administration.
Acetaminophen:
Acetaminophen in therapeutic doses rarely causes adverse reactions. The most serious adverse reaction is hepatoxicity from overdosage (see OVERDOSAGE). Thrombocytopenia, leukopenia, pancytopenia, neutropenia, thrombocytopenic purpura, and agranulocytosis have been reported in patients receiving acetaminophen or p-aminophenol derivatives. Hypersensitivity reactions including urticarial or erythematous skin reactions, laryngeal edema, angioedema, or anaphylactoid reactions are rare.
Caffeine:
Adverse reactions associated with caffeine use include anxiety, anxiety neurosis, excitement, headaches, insomnia, irritability, lightheadedness, restlessness, tenseness, tremor, extrasystoles, palpitations, tachycardia, diarrhea, nausea, stomach pain, vomiting, diuresis, urticaria, scintillating scotoma, and tinnitus.

Postmarketing Experience

- Serotonin syndrome: Cases of serotonin syndrome, a potentially life-threatening condition, have been reported during concomitant use of opioids with serotonergic drugs.
- Adrenal insufficiency: Cases of adrenal insufficiency have been reported with opioid use, more often following greater than one month of use.
- Anaphylaxis: Anaphylaxis has been reported with ingredients contained in TREZIX™.
- Androgen deficiency: Cases of androgen deficiency have occurred with chronic use of opioids [see CLINICAL PHARMACOLOGY].

Postmarketing Experience

- serotonin syndrome
- adrenal insufficiency

Androgen deficiency
Chronic use of opioids may influence the hypothalamic-pituitary-gonadal axis, leading to androgen deficiency that may manifest as symptoms of hypogonadism, such as impotence, erectile dysfunction, or amenorrhea. The causal role of opioids in the
syndrome of hypogonadism is unknown because the various medical, physical, lifestyle, and psychological stressors that may influence gonadal hormone levels have not been adequately controlled for in studies conducted to date. Patients presenting with symptoms of androgen deficiency should undergo laboratory evaluation.

DRUG ABUSE AND DEPENDENCE

Controlled Substance
TREZIX™ contains dihydrocodeine bitartrate, a Schedule III controlled substance.
Abuse
TREZIX™ contains dihydrocodeine bitartrate, a substance with a high potential for abuse similar to other Schedule III opioids. TREZIX™ can be abused and is subject to misuse, addiction, and criminal diversion [see WARNINGS].

All patients treated with opioids require careful monitoring for signs of abuse and addiction, since use of opioid analgesic products carries the risk of addiction even under appropriate medical use.
Prescription drug abuse is the intentional non-therapeutic use of a prescription drug, even once, for its rewarding psychological or physiological effects.
Drug addiction is a cluster of behavioral, cognitive, and physiological phenomena that develop after repeated substance use and includes: a strong desire to take the drug, difficulties in controlling its use, persisting in its use despite harmful consequences, a higher priority given to drug use than to other activities and obligations, increased tolerance, and sometimes a physical withdrawal.
“Drug-seeking” behavior is very common in persons with substance use disorders. Drug-seeking tactics include emergency calls or visits near the end of office hours, refusal to undergo appropriate examination, testing, or referral, repeated “loss” of prescriptions, tampering with prescriptions and reluctance to provide prior medical records or contact information for other treating health care provider(s). “Doctor shopping” (visiting multiple prescribers) to obtain additional prescriptions is common among drug abusers and people suffering from untreated addiction. Preoccupation with achieving adequate pain relief can be appropriate behavior in a patient with poor pain control.
Abuse and addiction are separate and distinct from physical dependence and tolerance. Health care providers should be aware that addiction may not be accompanied by concurrent tolerance and symptoms of physical dependence in all addicts. In addition, abuse of opioids can occur in the absence of true addiction.
TREZIX™, like other opioids, can be diverted for non-medical use into illicit channels of distribution. Careful record keeping of prescribing information, including quantity, frequency, and renewal requests, as required by state and federal law, is strongly advised.
Proper assessment of the patient, proper prescribing practices, periodic re-evaluation of therapy, and proper dispensing and storage are appropriate measures that help to limit abuse of opioid drugs.

Risks Specific to Abuse of TREZIX™
TREZIX™ is for oral use only. Abuse of TREZIX™ poses a risk of overdose and death. The risk is increased with concurrent use of TREZIX™ with alcohol and other central nervous system depressants.

Parenteral drug abuse is commonly associated with transmission of infectious diseases such as hepatitis and HIV.

Dependence
Both tolerance and physical dependence can develop during chronic opioid therapy. Tolerance is the need for increasing doses of opioids to maintain a defined effect such as analgesia (in the absence of disease progression or other external factors). Tolerance may occur to both the desired and undesired effects of drugs, and may develop at different rates for different effects.
Physical dependence results in withdrawal symptoms after abrupt discontinuation or a significant dosage reduction of a drug. Withdrawal also may be precipitated through the administration of drugs with opioid antagonist activity (e.g., naloxone, nalmefene), mixed agonist/antagonist
analgesics (pentazocine, butorphanol, nalbuphine), or partial agonists (buprenorphine). Physical dependence may not occur to a clinically significant degree until after several days to weeks of
continued opioid usage.
TREZIX™ should not be abruptly discontinued [see DOSAGE AND ADMINISTRATION]. If TREZIX™ is abruptly discontinued in a physicallydependent patient, a withdrawal syndrome may occur. Some or all of the following can characterize this syndrome: restlessness, lacrimation, rhinorrhea, yawning, perspiration, chills, myalgia, and mydriasis. Other signs and symptoms also may develop, including: irritability, anxiety, backache, joint pain, weakness, abdominal cramps, insomnia, nausea, anorexia, vomiting, diarrhea, or increased blood pressure, respiratory rate, or heart rate.
Infants born to mothers physically dependent on opioids will also be physically dependent and may exhibit respiratory difficulties and withdrawal signs [see PRECAUTIONS; Pregnancy].

OVERDOSAGE

Following an acute overdosage with TREZIX™ (acetaminophen, caffeine, and dihydrocodeine bitartrate) capsules, toxicity may result from the dihydrocodeine or the acetaminophen. Toxicity due to the caffeine is less likely, due to the relatively small amounts in this formulation.

Clinical Presentation
Acute overdose with TREZIX™ can be manifested by respiratory depression,
somnolence progressing to stupor or coma, skeletal muscle flaccidity, cold and clammy skin,constricted pupils, and, in some cases, pulmonary edema, bradycardia, hypotension, partial or complete airway obstruction, atypical snoring, and death. Marked mydriasis rather than miosis may be seen with hypoxia in overdose situations.

Signs and Symptoms
Toxicity from dihydrocodeine poisoning includes the opioid triad of: pinpoint pupils, respiratory depression, and loss of consciousness. Convulsions, cardiovascular collapse, and death may occur. A single case of acute rhabdomyolysis associated with an overdose of dihydrocodeine has been reported. In acetaminophen overdosage: dose-dependent potentially fatal hepatic necrosis is the most serious adverse effect. Renal tubular necrosis, hypoglycemic coma, and coagulation defects may also occur. Early symptoms following a potentially hepatotoxic overdose may include: nausea, vomiting, diaphoresis, and general malaise. Clinical and laboratory evidence of hepatic toxicity may not be apparent until 48 to 72 hours post-ingestion. Acute caffeine poisoning may cause insomnia, restlessness, tremor, delirium, tachycardia, and extrasystoles.

Because overdose information on this combination product is limited, it is unclear which of the signs and symptoms of toxicity would manifest in any particular overdose situation.
Treatment of Overdose
A single or multiple drug overdose with TREZIX™ (acetaminophen, caffeine and dihydrocodeine bitartrate) capsules is a potentially lethal polydrug overdose, and consultation with a regional poison control center is recommended.

In case of overdose, priorities are the reestablishment of a patent and protected airway and institution of assisted or controlled ventilation, if needed. Employ other supportive measures (including oxygen and vasopressors) in the management of circulatory shock and pulmonary edema as indicated. Cardiac arrest or arrhythmias will require advanced life-support techniques.

The opioid antagonists, naloxone or nalmefene, are specific antidotes to respiratory depression resulting from opioid overdose. For clinically significant respiratory or circulatory depression secondary to TREZIX™ overdose, administer an opioid antagonist. Opioid antagonists should not be administered in the absence of clinically significant respiratory or circulatory depression secondary to TREZIX™ overdose.

Because the duration of opioid reversal is expected to be less than the duration of action of dihydrocodeine bitartrate in TREZIX™ , carefully monitor the patient until spontaneous respiration is reliably re-established. If the response to an opioid antagonist is suboptimal or only brief in nature, administer additional antagonist as directed by the product’s prescribing information.

In an individual physically dependent on opioids, administration of the recommended usual dosage of the antagonist will precipitate an acute withdrawal syndrome. The severity of the withdrawal symptoms experienced will depend on the degree of physical dependence and the dose of the antagonist administered. If a decision is made to treat serious respiratory depression in the physically dependent patient, administration of the antagonist should be begun with care and by titration with smaller than usual doses of the antagonist.

For respiratory depression due to unusual sensitivity to dihydrocodeine, parenteral naloxone is a specific and effective antagonist.

Gastric decontamination with activated charcoal should be administered just prior to N-acetylcysteine (NAC) to decrease systemic absorption if acetaminophen ingestion is known or suspected to have occurred within a few hours of presentation.

Serum acetaminophen levels should be obtained immediately if the patient presents 4 hours or more after ingestion to assess potential risk of hepatotoxicity; acetaminophen levels drawn less than 4 hours post-ingestion may be misleading. To obtain the best possible outcome, NAC should be administered as soon as possible where impending or evolving liver injury is suspected. Intravenous NAC may be administered when circumstances preclude oral administration.

Vigorous supportive therapy is required in severe intoxication. Procedures to limit the continuing absorption of the drug must be readily performed since the hepatic injury is dose dependent and occurs early in the course of intoxication.

DOSAGE AND ADMINISTRATION

Important Dosage and Administration Instructions
Use the lowest effective dosage for the shortest duration consistent with individual patient treatment goals [see WARNINGS].

Initiate the dosing regimen for each patient individually, taking into account the patient's severity of pain, patient response, prior analgesic treatment experience, and risk factors for addiction, abuse, and misuse [see WARNINGS].

Monitor patients closely for respiratory depression, especially within the first 24-72 hours of initiating therapy and following dosage increases with TREZIX™ and adjust the dosage accordingly [see WARNINGS].

Initial Dosage
Initiating treatment with TREZIX™
The usual adult dosage is two (2) TREZIX™ (acetaminophen, caffeine, and dihydrocodeine bitartrate) capsules orally every four (4) hours, as needed. No more than five (5) doses, or ten (10) capsules should be taken in a 24-hour period.

Conversion from Other Opioids to TREZIX™
There is inter-patient variability in the potency of opioid drugs and opioid formulations. Therefore, a conservative approach is advised when determining the total daily dosage of TREZIX™. It is safer to underestimate a patient’s 24-hour TREZIX™ dosage than to overestimate the 24-hour TREZIX™ dosage and manage an adverse reaction due to overdose.

Titration and Maintenance of Therapy
Individually titrate TREZIX™ to a dose that provides adequate analgesia and minimizes adverse reactions. Continually reevaluate patients receiving TREZIX™ to assess the maintenance of pain control and the relative incidence of adverse reactions, as well as monitoring for the development of addiction, abuse, or misuse [see WARNINGS]. Frequent communication is important among the prescriber, other members of the healthcare team, the patient, and the caregiver/family during periods of changing analgesic requirements, including initial titration.

If the level of pain increases after dosage stabilization, attempt to identify the source of increased pain before increasing the TREZIX™ dosage. If unacceptable opioid-related adverse reactions are observed, consider reducing the dosage. Adjust the dosage to obtain an appropriate balance between management of pain and opioid-related adverse reactions.

Discontinuation of TREZIX™
When a patient who has been taking TREZIX™ regularly and may be physically dependent no longer requires therapy with TREZIX™, taper the dose gradually, by 25% to 50% every 2 to 4 days, while monitoring carefully for signs and symptoms of withdrawal. If the patient develops these signs or symptoms, raise the dose to the previous level and taper more slowly, either by increasing the interval between decreases, decreasing the amount of change in dose, or both. Do not abruptly discontinue TREZIX™ in a physically-dependent patient [see WARNINGS, DRUG ABUSE AND DEPENDENCE].

HOW SUPPLIED

TREZIX™ capsules, containing acetaminophen 320.5 mg, caffeine 30 mg and dihydrocodeine bitartrate 16 mg, are supplied in bottles of 100 capsules (NDC #66992-840-10).

Capsules are imprinted “TREZIX” on the red cap in white ink.

Store at 20°C to 25°C (68°F to 77°F). [see USP Controlled Room Temperature].

Dispense in a tight, light-resistant container with a child-resistant closure. Protect from moisture.

Rx Only

Manufactured for:
WraSer Pharmaceuticals LLC
Ridgeland, MS 39157

13001 Rev. 4/2017

Physician’s Desk Reference® is the registered trademark of Thomson Healthcare, Inc.

Medication Guide
Trezix (Tre~zix)
Capsules, CIII

Trezix is:

- A strong prescription pain medicine that contains an opioid (narcotic) that is used to manage moderate to moderately severe pain, when otherpain treatments such as non-opioid pain medicines do not treat your pain well enough or you cannot tolerate them.
- An opioid pain medicine that can put you at risk for overdose and death. Even if you take your dose correctly as prescribed you are at risk for opioid addiction, abuse, and misuse that can lead to death.

Important information about Trezix:

- Get emergency help right away if you take too much Trezix (overdose). When you first start taking Trezix, when your dose is changed, or if you take too much (overdose), serious or life-threatening breathing problems that can lead to death may occur.
- Taking Trezix with other opioid medicines, benzodiazepines, alcohol, or other central nervous system depressants (including street drugs) can cause severe drowsiness, decrease awareness, breathing problems, coma and death.
- Never give anyone else your Trezix. They could die from taking it. Store Trezix away from children and in a safe place to prevent stealing or abuse. Selling or giving away Trezix is against the law.

Important Information Guiding Use in Pediatric Patients:

- Do not give Trezix to a child younger than 12 years of age.

- Do not give Trezix to a child younger than 18 years of age after surgery to remove the tonsils and/or adenoids.

- Avoid giving Trezix to children between 12 to 18 years of age who have risk factors for breathing problems such as obstructive sleep apnea, obesity, or underlying lung problems

Do not take Trezix if you have:

- severe asthma, trouble breathing, or other lung problems.
- a bowel blockage or have narrowing of the stomach or intestines.
- previously had an allergic reaction to dihydrocodeine or acetaminophen.

Before taking Trezix, tell your healthcare provider if you have a history of:

- head injury, seizures ● liver, kidney, thyroid problems
- problems urinating ● pancreas or gallbladder problems
- abuse of street or prescription drugs, alcohol addiction, or mental health problems.
- have been told by your healthcare provider that you are a “rapid metabolizer” of certain medicines.

Tell your healthcare provider if you are:

- pregnant or planning to become pregnant. Prolonged use of Trezix during pregnancy can cause withdrawal symptoms in your newborn baby that could be life-threatening if not recognized and treated.
- breastfeeding. Not recommended; may harm your baby.
- taking prescription or over-the-counter medicines, vitamins, or herbal supplements. Taking Trezix with certain other medicines can cause serious side effects that could lead to death.

When taking Trezix:

- Do not change your dose. Take Trezix exactly as prescribed by your healthcare provider. Use the lowest dose possible for the shortest time needed.
- Take your prescribed dose of 2 Trezix capsules orally every 4 hours, as needed. Do not take more than your prescribed dose. If you miss a dose, take your next dose at your usual time.

- Call your healthcare provider if the dose you are taking does not control your pain.
- If you have been taking Trezix regularly, do not stop taking Trezix without talking to your healthcare provider.

- After you stop taking Trezix, dispose the unused Trezix in accordance with local state guidelines and/or regulations.

While taking Trezix DO NOT:

- Drive or operate heavy machinery, until you know how Trezix affects you. Trezix can make you sleepy, dizzy, or lightheaded.
- Drink alcohol or use prescription or over-the-counter medicines that contain alcohol. Using products containing alcohol during treatment with Trezix may cause you to overdose and die.

The possible side effects of Trezix:

- constipation, nausea, sleepiness, vomiting, tiredness, headache, dizziness, abdominal pain. Call your healthcare provider if you have any of these symptoms and they are severe.

Get emergency medical help if you have:

- trouble breathing, shortness of breath, fast heartbeat, chest pain, swelling of your face, tongue, or throat, extreme drowsiness, light-headedness when changing positions, feeling faint, agitation, high body temperature, trouble walking, stiff muscles, or mental changes such as confusion.

These are not all the possible side effects of Trezix. Call your doctor for medical advice about side effects. You may report side effects to FDA at 1-800-FDA-1088. For more information go to dailymed.nlm.nih.gov

Manufactured for: WraSer Pharmaceuticals, 121 Marketridge Drive, Ridgeland, MS 39157, www.wraser.com or call1-888-252-3901

This Medication Guide has been approved by the U.S. Food and Drug Administration. Issued: 12/2017

Trezix 100 Count Bottle

NDC 66992-840-10

TREZIXTM CIII

(acetaminophen, caffeine and dihydrocodeine bitartrate capsules 320.5mg/30mg/16mg)

Rx ONLY

100 CAPSULES

DESCRIPTION:
Each red capsule contains:
Acetaminophen .................................. 320.5 mg
Caffeine ................................................... 30 mg
Dihydrocodeine Bitartrate ....................... 16 mg

USUAL DOSAGE: See package insert for full prescribing information.

WARNING: Keep this and all medications out of the reach of children.

ATTENTION DISPENSER: Dispense the accompanying Medication Guide to each patient.

For additional Medication Guides, please visit www.Trezixrx.com

Dispense in a tight, light-resistant container with a child-resistant closure. Store at 20° to 25°C (68° to 77°F) [see USP Controlled Room Temperature]. Protect from moisture.

Manufactured for:
WraSer Pharmaceuticals
Ridgeland, MS 39157
www.wraser.com

13001 Rev. 7/2017

WraSer PHARMACEUTICALS